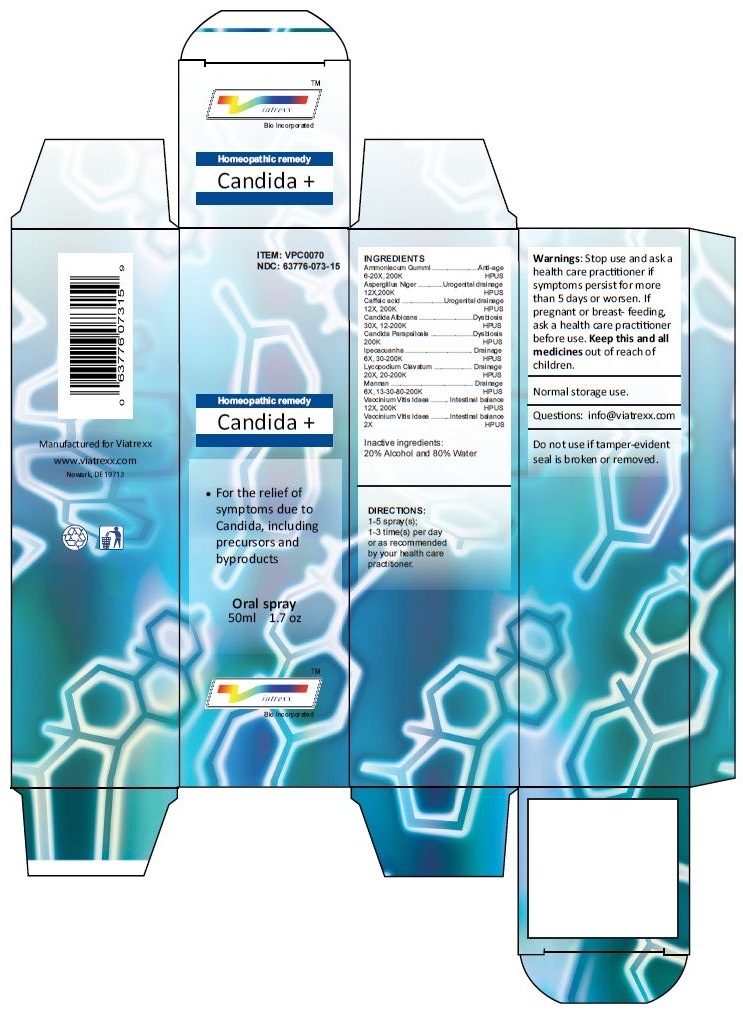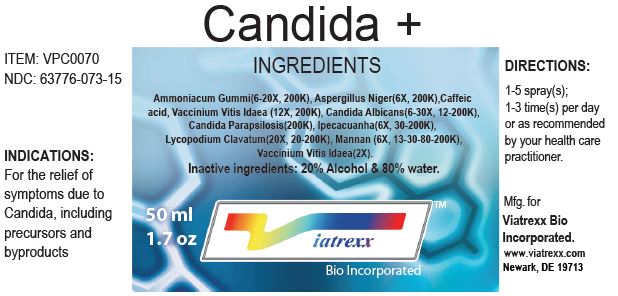 DRUG LABEL: Candida
NDC: 63776-073 | Form: SPRAY
Manufacturer: VIATREXX BIO INCORPORATED
Category: homeopathic | Type: HUMAN OTC DRUG LABEL
Date: 20221130

ACTIVE INGREDIENTS: AMMONIAC 200 [kp_C]/1 mL; ASPERGILLUS NIGER VAR. NIGER 200 [kp_C]/1 mL; CAFFEIC ACID 200 [kp_C]/1 mL; CANDIDA ALBICANS 200 [kp_C]/1 mL; CANDIDA PARAPSILOSIS 200 [kp_C]/1 mL; IPECAC 200 [kp_C]/1 mL; LYCOPODIUM CLAVATUM SPORE 200 [kp_C]/1 mL; YEAST MANNAN 200 [kp_C]/1 mL; VACCINIUM VITIS-IDAEA LEAF 200 [kp_C]/1 mL
INACTIVE INGREDIENTS: ALCOHOL; WATER

Candida +

Active Ingredients

Ammoniacum Gummi 6-20X 200K, Aspergillus Niger 12X 200K, Caffeic acid 12X 200K, Candida Albicans 30X 12-200K, Candida Parapsilosis 200K, Ipecacuanha 6X 30-200K, Lycopodium Clavatum 20X 20-200K, Mannan 6X 13-30-80-200K, Vaccinium Vitis Idaea 12X 200K, Vaccinium Vitis Idaea 2X

Purpose:

Ammoniacum Gummi | Anti-age
Aspergillus Niger | Urogenital drainage
Caffeic acid | Urogenital drainage
Candida Albicans | Dysbiosis
Candida Parapsilosis | Dysbiosis
Ipecacuanha | Drainage
Lycopodium Clavatum | Drainage
Mannan | Drainage
Vaccinium Vitis Idaea | Intestinal
Vaccinium Vitis Idaea | Intestinal

Uses

For the relief of symptoms due to Candida, including precursors and byproducts

Warnings

Stop use and ask a health care practitioner if symptoms persist for more than five days or worsen. If pregnant or breastfeeding, ask a health care practitioner before use.

Dosage

1-5 spray(s); 1-3 time(s) per day or as recommended by your health care practitioner.

KEEP OUT OF REACH OF CHILDREN

Keep this and all medicines out of reach of children.

Other Ingredients

Alcohol and Water

Other Information

Normal storage use.
Do not use if tamper-evident seal is broken or removed.

Questions

info@viatrexx.com

Principal Display Panel

ITEM: VPC0070
NDC 63776-073-15
Homeopathic remedy
Candida +
• For the relief of symptoms due to Candida, including precursors and byproducts
Oral spray
50ml 1.7 oz
Viatrexx™ Bio Incorporated
Manufactured by Viatrexx
www.viatrexx.com
Newark, DE 19713

Candida +
50 mL
1.7 oz
Viatrexx™ Bio Incorporated
ITEM: VPC0070
NDC: 63776-073-15
INDICATIONS:
For the relief of symptoms due to Candida, including precursors and byproducts
DIRECTIONS:
1-5 spray(s); 1-3 time(s) per day or as recommended by your health care practitioner.
Mfg. for
Viatrexx Bio Incorporated.
www.viatrexx.com
Newark, DE 19713